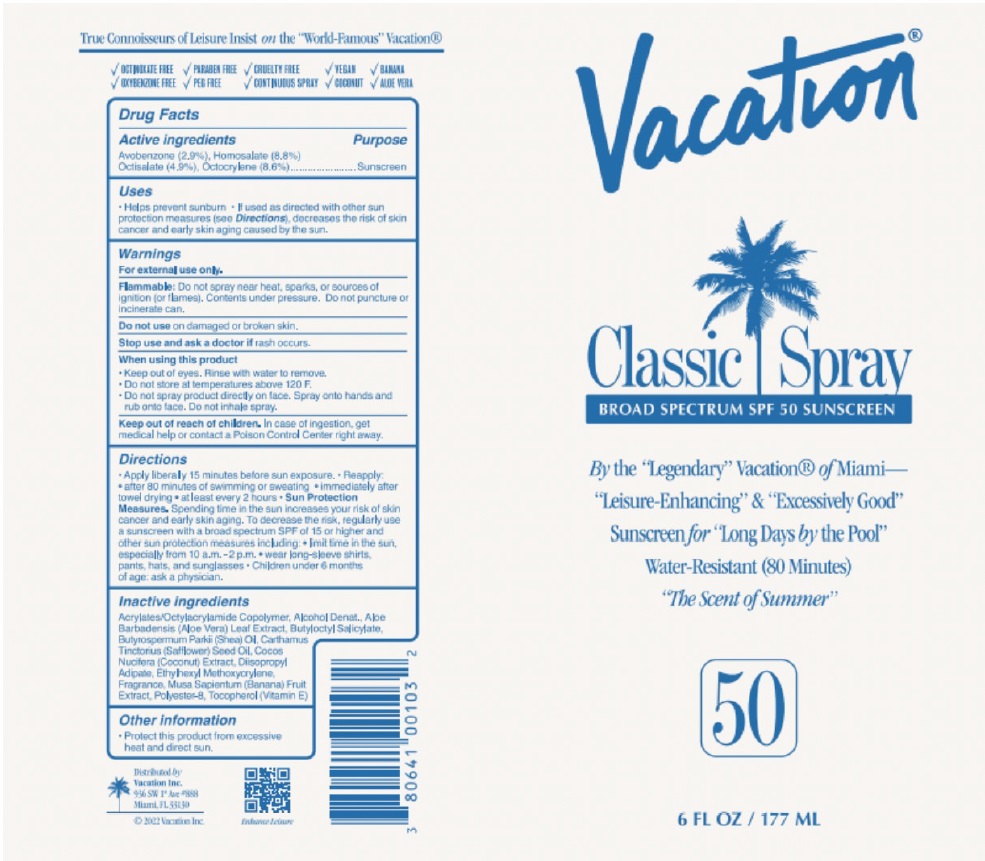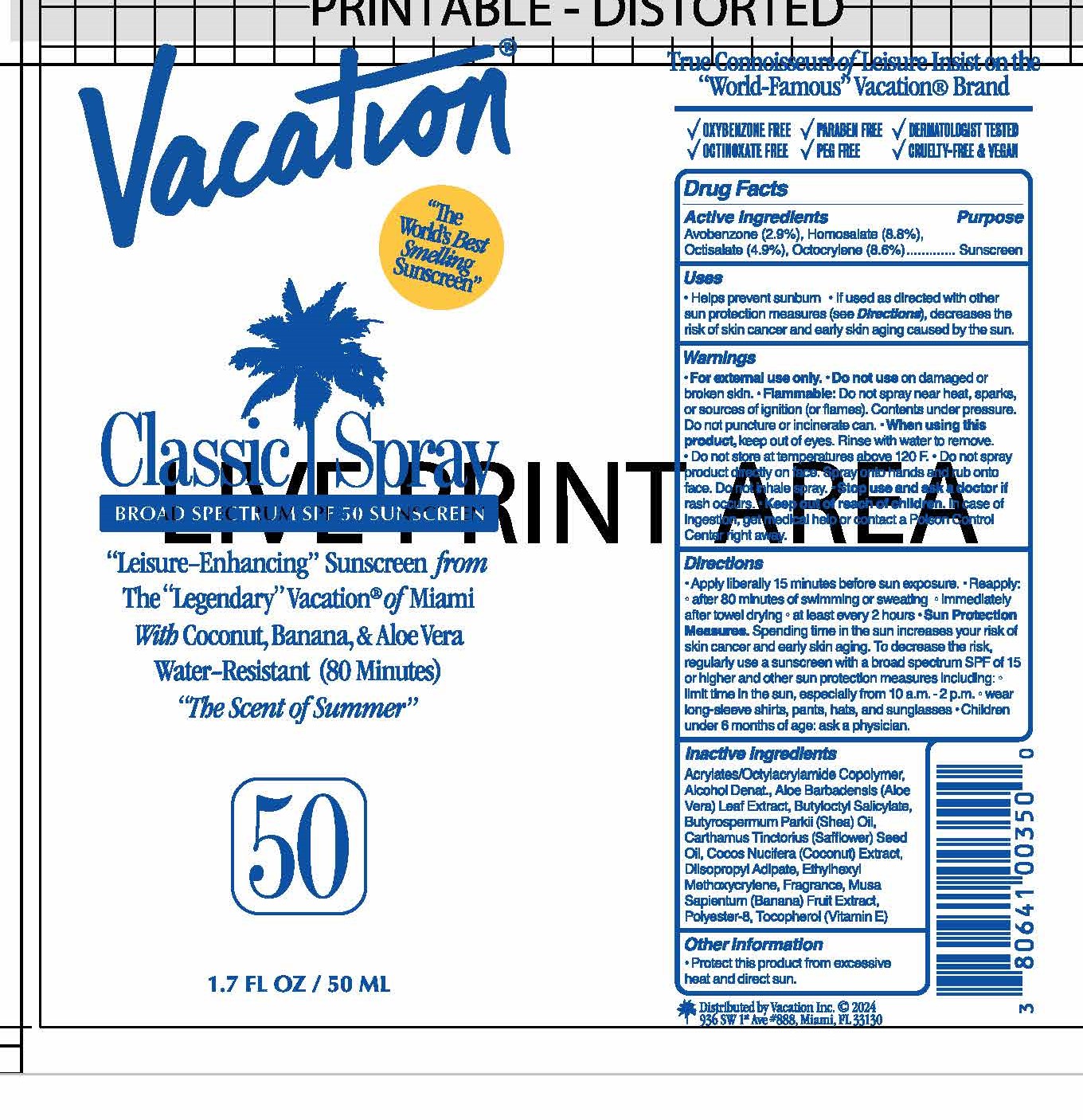 DRUG LABEL: Vacation SPF 50 Classic
NDC: 80641-007 | Form: SPRAY
Manufacturer: Vacation Inc.
Category: otc | Type: HUMAN OTC DRUG LABEL
Date: 20250224

ACTIVE INGREDIENTS: HOMOSALATE 8.8 g/100 mL; AVOBENZONE 2.9 g/100 mL; OCTOCRYLENE 8.6 g/100 mL; OCTISALATE 4.9 g/100 mL
INACTIVE INGREDIENTS: ETHYLHEXYL METHOXYCRYLENE; BANANA; TOCOPHEROL; ACRYLATE/ISOBUTYL METHACRYLATE/N-TERT-OCTYLACRYLAMIDE COPOLYMER (75000 MW); ALOE VERA LEAF; SHEANUT OIL; SAFFLOWER OIL; COCONUT; ALCOHOL; BUTYLOCTYL SALICYLATE; POLYESTER-8 (1400 MW, CYANODIPHENYLPROPENOYL CAPPED); DIISOPROPYL ADIPATE

Vacation SPF 50 Classic Spray

Active Ingredients

Avobenzone 2.9%

Homosalate 8.8%

Octisalate 4.9%

Octocrylene 7.6%

Purpose

Sunscreen

Uses

Helps prevent sunburn
If used as directed with other sun protection measures (see Directions), decreases the risk of skin cancer and early skin aging caused by the sun.

Warnings

For external use only

Flammable. Do not spray near heat, sparks, or sources of ignition (or flames). Contents under pressure. Do not puncture or incinerate can.

Do not use on damaged or broken skin.

Stop use and ask a doctor if rash occurs.

When using this product

-Keep out of eyes. Rinse with water to remove.

-Do not store at temperatures above 120 F

-Do not spray product directly on face. Spay onto hands and rub into face. Do not inhale spray.

Keep out of reach of children. If swallowed, get medical help or contact a Poison Control Center right away.

Directions

Apply liberally 15 minutes before sun exposure.

Reapply:

-After 80 minutes of swimming or sweating.
-Immediately after towel drying
-At least every 2 hours

Sun Protection Measure: Spending time in the sun increases your risk of skin cancer and early skin aging. To decrease this risk, regularly use a sunscreen with a broad spectrum SPF value of 15 or higher and other sun protection measures including:

-Limit time in the sun, especially from 10 a.m. to 2 p.m.
-Wear long-sleeved shirts, pants, hats, and sun glasses.

Children under 6 months: ask a doctor.

Inactive Ingredients

Acrylates/Octylacrylamide Copolymer, Alcohol Denat., Aloe Barbadensis (Aloe Vera) Leaf Extract, Butyloctyl Salicylate, Butyrospermum Parkii (Shea) Oil, Carthamus Tinctorius (Safflower) Seed Oil, Cocos Nucifera (Coconut) Extract, Diisopropyl Adipate, Ethylhexyl Methoxycrylene, Fragrance, Musa Sapientum (Banana) Fruit Extract, Polyester-8, Tocopherol (Vitamin E)

Other Information

Protect this product from excessive heat and direct sun